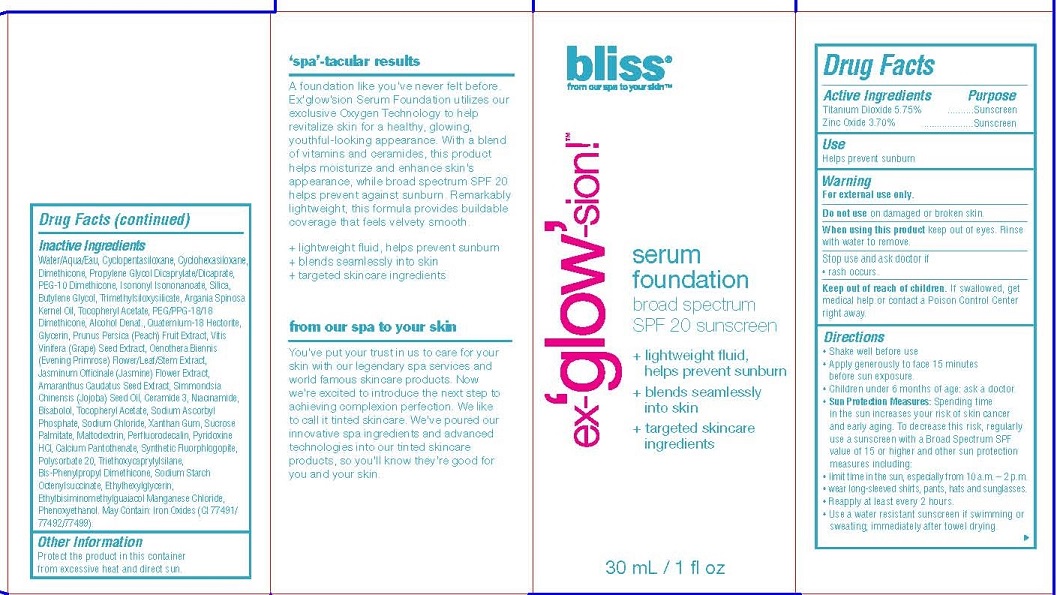 DRUG LABEL: EX-GLOW-SION
NDC: 69863-103 | Form: LOTION
Manufacturer: HATCHBEAUTY PRODUCTS LLC
Category: otc | Type: HUMAN OTC DRUG LABEL
Date: 20160221

ACTIVE INGREDIENTS: TITANIUM DIOXIDE 5.75 g/100 mL; ZINC OXIDE 3.7 g/100 mL
INACTIVE INGREDIENTS: WATER; CYCLOMETHICONE 5; CYCLOMETHICONE 6; DIMETHICONE; PROPYLENE GLYCOL DICAPRYLATE/DICAPRATE; PEG-10 DIMETHICONE (600 CST); ISONONYL ISONONANOATE; SILICON; BUTYLENE GLYCOL; TRIMETHYLSILOXYSILICATE (M/Q 0.6-0.8); ARGAN OIL; PEG/PPG-18/18 DIMETHICONE; .ALPHA.-TOCOPHEROL ACETATE; ALCOHOL; QUATERNIUM-18 HECTORITE; GLYCERIN; PEACH JUICE; VITIS VINIFERA WHOLE; OENOTHERA BIENNIS; JASMINUM OFFICINALE FLOWER; AMARANTHUS CAUDATUS SEED; JOJOBA OIL; CERAMIDE 3; NIACINAMIDE; .ALPHA.-BISABOLOL, (+/-)-; SODIUM ASCORBYL PHOSPHATE; SODIUM CHLORIDE; XANTHAN GUM; SUCROSE PALMITATE; MALTODEXTRIN; PERFLUNAFENE; PYRIDOXINE HYDROCHLORIDE; CALCIUM PANTOTHENATE; POLYSORBATE 20; TRIETHOXYCAPRYLYLSILANE; BIS-PHENYLPROPYL DIMETHICONE (15 CST); SODIUM STARCH GLYCOLATE TYPE A CORN; ETHYLHEXYLGLYCERIN; ETHYLBISIMINOMETHYLGUAIACOL MANGANESE CHLORIDE; PHENOXYETHANOL; FERRIC OXIDE RED; FERROSOFERRIC OXIDE; FERRIC OXIDE YELLOW

ACTIVE INGREDIENTS

TITANIUM DIOXIDE 5.75%

ZINC OXIDE 3.70%

PURPOSE

SUNSCREEN

USES

HELPS PREVENT SUNBURN

WARNINGS

• For external use only.
• DO NOT USE ON DAMAGED OR BROKEN SKIN.

WHEN USING THIS PRODUCT KEEP OUT OF EYES. RINSE WITH WATER TO REMOVE.

STOP USE AND ASK A DOCTOR IF RASH OCCURS.

• Keep out of reach of children. If product is swallowed, get medical help or contact a Poison Control Center right away.

Directions

- Shake well before use
- Apply generously to face 15 minutes before sun exposure.
- Children under 6 months of age: ask a doctor.
- Sun Protection Measures: Spending time in the sun increases your risk of skin cancer and early aging. To decrease this risk, regularly use a sunscreen with a Broad Spectrum SPF value of 15 or higher and other sun protection measures including:

• limit time in the sun, especially from 10 a.m. – 2 p.m.
• wear long-sleeved shirts, pants, hats and sunglasses.
• Reapply at least every 2 hours.
• Use a water resistant sunscreen if swimming or sweating; immediately after towel drying.

Inacitve Ingredients

Water/Aqua/Eau, Cyclopentasiloxane, Cyclohexasiloxane, Dimethicone, Propylene Glycol Dicaprylate/Dicaprate, PEG-10 Dimethicone, Isononyl Isononanoate, Silica, Butylene Glycol, Trimethylsiloxysilicate, Argania Spinosa Kernel Oil, Tocopheryl Acetate, PEG/PPG-18/18 Dimethicone, Alcohol Denat., Quaternium-18 Hectorite, Glycerin, Prunus Persica (Peach) Fruit Extract, Vitis Vinifera (Grape) Seed Extract, Oenothera Biennis (Evening Primrose) Flower/Leaf/Stem Extract, Jasminum Officinale (Jasmine) Flower Extract, Amaranthus Caudatus Seed Extract, Simmondsia Chinensis (Jojoba) Seed Oil, Ceramide 3, Niacinamide, Bisabolol, Tocopheryl Acetate, Sodium Ascorbyl Phosphate, Sodium Chloride, Xanthan Gum, Sucrose Palmitate, Maltodextrin, Perfluorodecalin, Pyridoxine HCl, Calcium Pantothenate, Synthetic Fluorphlogopite, Polysorbate 20, Triethoxycaprylylsilane, Bis-Phenylpropyl Dimethicone, Sodium Starch Octenylsuccinate, Ethylhexylglycerin,
Ethylbisiminomethylguaiacol Manganese Chloride, Phenoxyethanol. May Contain: Iron Oxides (CI 77491/77492/77499).

OTHER INFORMATION

PROTECT THIS PRODUCT IN THIS CONTAINER FROM EXCESSIVE HEAT AND DIRECT SUN.